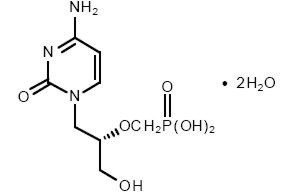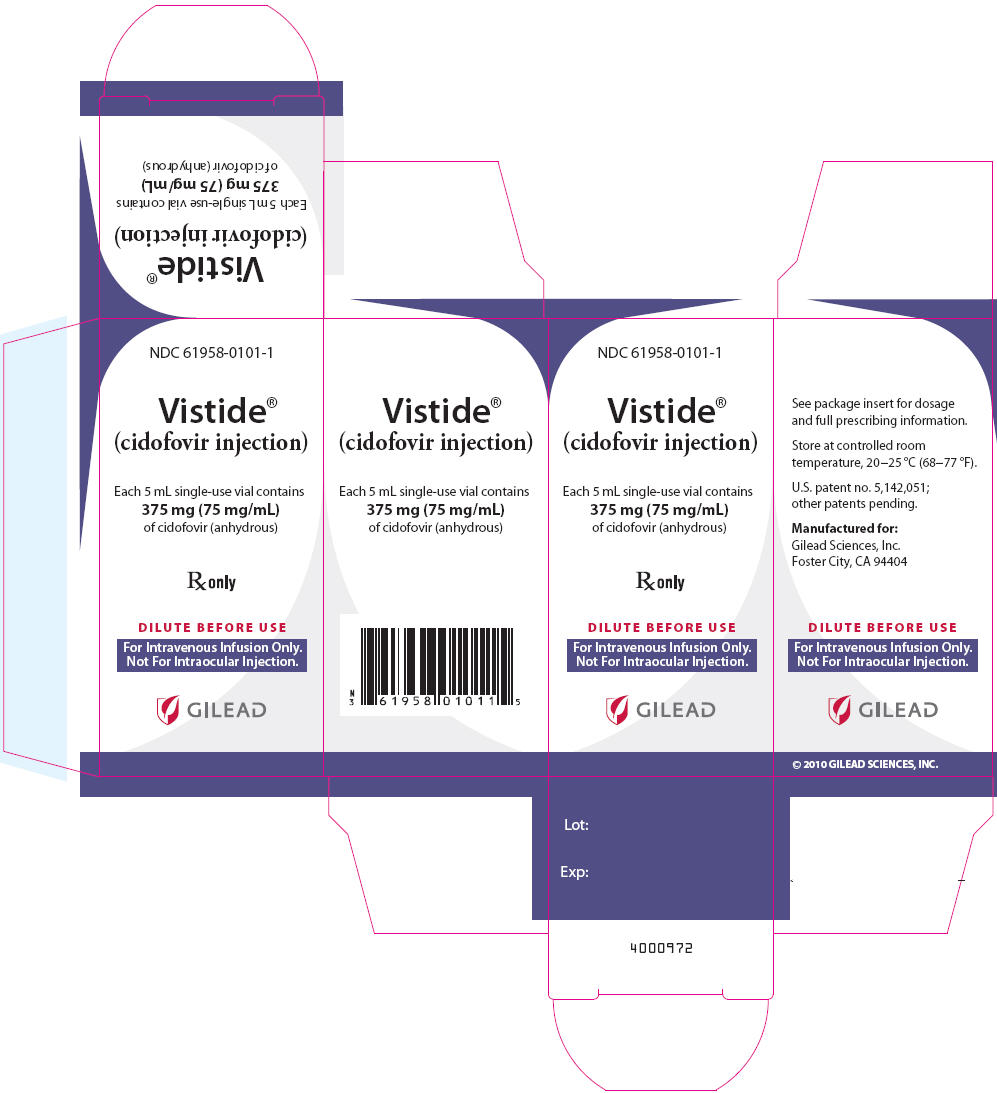 DRUG LABEL: Vistide
NDC: 61958-0101 | Form: INJECTION
Manufacturer: Gilead Sciences, Inc.
Category: prescription | Type: HUMAN PRESCRIPTION DRUG LABEL
Date: 20130924

ACTIVE INGREDIENTS: CIDOFOVIR 75 mg/1 mL
INACTIVE INGREDIENTS: WATER; SODIUM HYDROXIDE; HYDROCHLORIC ACID

VISTIDE® (cidofovir injection)

Rx only.

FOR INTRAVENOUS INFUSION ONLY.
NOT FOR INTRAOCULAR INJECTION.

WARNING

RENAL IMPAIRMENT IS THE MAJOR TOXICITY OF VISTIDE. CASES OF ACUTE RENAL FAILURE RESULTING IN DIALYSIS AND/OR CONTRIBUTING TO DEATH HAVE OCCURRED WITH AS FEW AS ONE OR TWO DOSES OF VISTIDE. TO REDUCE POSSIBLE NEPHROTOXICITY, INTRAVENOUS PREHYDRATION WITH NORMAL SALINE AND ADMINISTRATION OF PROBENECID MUST BE USED WITH EACH VISTIDE INFUSION. RENAL FUNCTION (SERUM CREATININE AND URINE PROTEIN) MUST BE MONITORED WITHIN 48 HOURS PRIOR TO EACH DOSE OF VISTIDE AND THE DOSE OF VISTIDE MODIFIED FOR CHANGES IN RENAL FUNCTION AS APPROPRIATE (SEE DOSAGE AND ADMINISTRATION). VISTIDE IS CONTRAINDICATED IN PATIENTS WHO ARE RECEIVING OTHER NEPHROTOXIC AGENTS.

NEUTROPENIA HAS BEEN OBSERVED IN ASSOCIATION WITH VISTIDE TREATMENT. THEREFORE, NEUTROPHIL COUNTS SHOULD BE MONITORED DURING VISTIDE THERAPY.

VISTIDE IS INDICATED ONLY FOR THE TREATMENT OF CMV RETINITIS IN PATIENTS WITH ACQUIRED IMMUNODEFICIENCY SYNDROME.

IN ANIMAL STUDIES CIDOFOVIR WAS CARCINOGENIC, TERATOGENIC AND CAUSED HYPOSPERMIA (SEE CARCINOGENESIS, MUTAGENESIS, & IMPAIRMENT OF FERTILITY).

DESCRIPTION

VISTIDE® is the brand name for cidofovir injection. The chemical name of cidofovir is 1-[(S)-3-hydroxy-2-(phosphonomethoxy)propyl]cytosine dihydrate (HPMPC), with the molecular formula of C8H14N3O6P•2H2O and a molecular weight of 315.22 (279.19 for anhydrous). The chemical structure is:

Cidofovir is a white crystalline powder with an aqueous solubility of ≥ 170 mg/mL at pH 6–8 and a log P (octanol/aqueous buffer, pH 7.1) value of -3.3.

VISTIDE is a sterile, hypertonic aqueous solution for intravenous infusion only. The solution is clear and colorless. It is supplied in clear glass vials, each containing 375 mg of anhydrous cidofovir in 5 mL aqueous solution at a concentration of 75 mg/mL. The formulation is pH-adjusted to 7.4 with sodium hydroxide and/or hydrochloric acid and contains no preservatives. The appropriate volume of VISTIDE must be removed from the single-use vial and diluted prior to administration (see DOSAGE AND ADMINISTRATION).

MICROBIOLOGY

Mechanism of Action

Cidofovir suppresses cytomegalovirus (CMV) replication by selective inhibition of viral DNA synthesis. Biochemical data support selective inhibition of CMV DNA polymerase by cidofovir diphosphate, the active intracellular metabolite of cidofovir. Cidofovir diphosphate inhibits herpesvirus polymerases at concentrations that are 8- to 600-fold lower than those needed to inhibit human cellular DNA polymerases alpha, beta, and gamma^(1, 2, 3). Incorporation of cidofovir into the growing viral DNA chain results in reductions in the rate of viral DNA synthesis.

In Vitro Susceptibility

Cidofovir is active in vitro against a variety of laboratory and clinical isolates of CMV and other herpesviruses (Table 1). Controlled clinical studies of efficacy have been limited to patients with AIDS and CMV retinitis.

Table 1. Cidofovir Inhibition of Virus Multiplication in Cell Culture
Virus | IC50 (µM)
Wild-type CMV Isolates | 0.5 – 2.8
HSV-1, HSV-2 | 12.7 – 31.7

Resistance

CMV isolates with reduced susceptibility to cidofovir have been selected in vitro in the presence of high concentrations of cidofovir^4. IC50 values for selected resistant isolates ranged from 7–15 µM.

There are insufficient data at this time to assess the frequency or the clinical significance of the development of resistant isolates following VISTIDE administration to patients.

The possibility of viral resistance should be considered for patients who show a poor clinical response or experience recurrent retinitis progression during therapy.

Cross Resistance

Cidofovir-resistant isolates selected in vitro following exposure to increasing concentrations of cidofovir were assessed for susceptibility to ganciclovir and foscarnet^4. All were cross resistant to ganciclovir, but remained susceptible to foscarnet. Ganciclovir- or ganciclovir/foscarnet-resistant isolates that are cross resistant to cidofovir have been obtained from drug naive patients and from patients following ganciclovir or ganciclovir/ foscarnet therapy. To date, the majority of ganciclovir-resistant isolates are UL97 gene product (phosphokinase) mutants and remain susceptible to cidofovir^5. Reduced susceptibility to cidofovir, however, has been reported for DNA polymerase mutants of CMV which are resistant to ganciclovir^6–9. To date, all clinical isolates which exhibit high level resistance to ganciclovir, due to mutations in both the DNA polymerase and UL97 genes, have been shown to be cross resistant to cidofovir. Cidofovir is active against some, but not all, CMV isolates which are resistant to foscarnet^10–12. The incidence of foscarnet-resistant isolates that are resistant to cidofovir is not known.

A few triple-drug resistant isolates have been described. Genotypic analysis of two of these triple-resistant isolates revealed several point mutations in the CMV DNA polymerase gene. The clinical significance of the development of these cross-resistant isolates is not known.

CLINICAL PHARMACOLOGY

PHARMACOKINETICS

VISTIDE must be administered with probenecid. The pharmacokinetics of cidofovir, administered both without and with probenecid, are described below.

The pharmacokinetics of cidofovir without probenecid were evaluated in 27 HIV-infected patients with or without asymptomatic CMV infection. Dose-independent pharmacokinetics were demonstrated after one hr infusions of 1.0 (n = 5), 3.0 (n = 10), 5.0 (n = 2) and 10.0 (n = 8) mg/kg (See Table 2 for pharmacokinetic parameters). There was no evidence of cidofovir accumulation after 4 weeks of repeated administration of 3 mg/kg/week (n = 5) without probenecid. In patients with normal renal function, approximately 80 to 100% of the VISTIDE dose was recovered unchanged in urine within 24 hr (n = 27). The renal clearance of cidofovir was greater than creatinine clearance, indicating renal tubular secretion contributes to the elimination of cidofovir.

The pharmacokinetics of cidofovir administered with probenecid were evaluated in 12 HIV-infected patients with or without asymptomatic CMV infection and 10 patients with relapsing CMV retinitis. Dose-independent pharmacokinetics were observed for cidofovir, administered with probenecid, after one hr infusions of 3.0 (n = 12), 5.0 (n = 6), and 7.5 (n = 4) mg/kg (See Table 2). Approximately 70 to 85% of the VISTIDE dose administered with concomitant probenecid was excreted as unchanged drug within 24 hr. When VISTIDE was administered with probenecid, the renal clearance of cidofovir was reduced to a level consistent with creatinine clearance, suggesting that probenecid blocks active renal tubular secretion of cidofovir.

Table 2. Cidofovir Pharmacokinetic Parameters Following 3.0 and 5.0 mg/kg Infusions, Without and With Probenecid [See DOSAGE AND ADMINISTRATION]
PARAMETERS | VISTIDE ADMINISTERED WITHOUT PROBENECID |  | VISTIDE ADMINISTERED WITH PROBENECID
 | 3 mg/kg (n = 10) | 5 mg/kg (n = 2) | 3 mg/kg (n = 12) | 5 mg/kg (n = 6)
AUC (µg∙hr/mL) | 20.0 ± 2.3 | 28.3 | 25.7 ± 8.5 | 40.8 ± 9.0
Cmax (end of infusion) (µg/mL) | 7.3 ± 1.4 | 11.5 | 9.8 ± 3.7 | 19.6 ± 7.2
Vdss (mL/kg) | 537 ± 126 (n = 12) |  | 410 ± 102 (n = 18)
Clearance (mL/min/1.73 m^2) | 179 ± 23.1 (n = 12) |  | 148 ± 38.8 (n = 18)
Renal Clearance (mL/min/1.73 m^2) | 150 ± 26.9 (n = 12) |  | 98.6 ± 27.9 (n = 11)

In vitro, cidofovir was less than 6% bound to plasma or serum proteins over the cidofovir concentration range 0.25 to 25 µg/mL. CSF concentrations of cidofovir following intravenous infusion of VISTIDE 5 mg/kg with concomitant probenecid and intravenous hydration were undetectable (< 0.1 µg/mL, assay detection threshold) at 15 minutes after the end of a 1 hr infusion in one patient whose corresponding serum concentration was 8.7 µg/mL.

DRUG-DRUG INTERACTIONS

Zidovudine

The pharmacokinetics of zidovudine were evaluated in 10 patients receiving zidovudine alone or with intravenous cidofovir (without probenecid). There was no evidence of an effect of cidofovir on the pharmacokinetics of zidovudine.

SPECIAL POPULATIONS

Renal Insufficiency

Pharmacokinetic data collected from subjects with creatinine clearance values as low as 11 mL/min indicate that cidofovir clearance decreases proportionally with creatinine clearance.

High-flux hemodialysis has been shown to reduce the serum levels of cidofovir by approximately 75%.

Initiation of therapy with VISTIDE is contraindicated in patients with serum creatinine > 1.5 mg/dL, a calculated creatinine clearance ≤ 55 mL/min, or a urine protein ≥ 100 mg/dL (equivalent to ≥2+ proteinuria) (See CONTRAINDICATIONS).

Geriatric/Gender/Race

The effects of age, gender, and race on cidofovir pharmacokinetics have not been investigated.

INDICATION AND USAGE

VISTIDE is indicated for the treatment of CMV retinitis in patients with acquired immunodeficiency syndrome (AIDS). THE SAFETY AND EFFICACY OF VISTIDE HAVE NOT BEEN ESTABLISHED FOR TREATMENT OF OTHER CMV INFECTIONS (SUCH AS PNEUMONITIS OR GASTROENTERITIS), CONGENITAL OR NEONATAL CMV DISEASE, OR CMV DISEASE IN NON-HIV-INFECTED INDIVIDUALS.

DESCRIPTION OF CLINICAL TRIALS

Three phase II/III controlled trials of VISTIDE have been conducted in HIV-infected patients with CMV retinitis.

Delayed Versus Immediate Therapy (Study 105)

In stage 1 of this open-label trial, conducted by the Studies of the Ocular Complications of AIDS (SOCA) Clinical Research Group, 29 previously untreated patients with peripheral CMV retinitis were randomized to either immediate treatment with VISTIDE (5 mg/kg once a week for 2 weeks, then 3 mg/kg every other week) or to have VISTIDE delayed until progression of CMV retinitis^13. In stage 2 of this trial, an additional 35 previously untreated patients with peripheral CMV retinitis were randomized to either immediate treatment with VISTIDE (5 mg/kg once a week for 2 weeks, then 5 mg/kg every other week), immediate treatment with VISTIDE (5 mg/kg once a week for 2 weeks, then 3 mg/kg every other week), or to have VISTIDE delayed until progression of CMV retinitis. Of the 64 patients in this study, 12 were randomized to 5 mg/kg maintenance therapy, 26 to 3 mg/kg maintenance therapy, and 26 to delayed therapy. Of the 12 patients enrolled in the 5 mg/kg maintenance group, 5 patients progressed, 5 patients discontinued therapy and 2 patients had no progression at study completion. Based on masked readings of retinal photographs, the median [95% confidence interval (CI)] time to retinitis progression was not reached (25, not reached) for the 5 mg/kg maintenance group. Median (95% CI) time to the alternative endpoint of retinitis progression or study drug discontinuation was 44 days (24, 207) for the 5 mg/kg maintenance group. Patients receiving 5 mg/kg maintenance had delayed time to retinitis progression compared to patients receiving 3 mg/kg maintenance or deferred therapy.

Delayed Versus Immediate Therapy (Study 106)

In an open-label trial, 48 previously untreated patients with peripheral CMV retinitis were randomized to either immediate treatment with VISTIDE (5 mg/kg once a week for 2 weeks, then 5 mg/kg every other week), or to have VISTIDE delayed until progression of CMV retinitis^14. Patient baseline characteristics and disposition are shown in Table 3. Of 25 and 23 patients in the immediate and delayed groups respectively, 23 and 21 were evaluable for retinitis progression as determined by retinal photography. Based on masked readings of retinal photographs, the median [95% confidence interval (CI)] times to retinitis progression were 120 days (40, 134) and 22 days (10, 27) for the immediate and delayed therapy groups, respectively. This difference was statistically significant. However, because of the limited number of patients remaining on treatment over time (3 of 25 patients received VISTIDE for 120 days or longer), the median time to progression for the immediate therapy group was difficult to precisely estimate. Median (95% CI) times to the alternative endpoint of retinitis progression or study drug discontinuation (including adverse events, withdrawn consent, and systemic CMV disease) were 52 days (37, 85) and 22 days (13, 27) for the immediate and delayed therapy groups, respectively. This difference was statistically significant. Time to progression estimates from this study may not be directly comparable to estimates reported for other therapies.

Table 3. Patient Characteristics and Disposition (Study 106)
 | Immediate Therapy | Delayed Therapy
 | (n = 25) | (n = 23)
Baseline Characteristics
Age (years) | 38 | 38
Sex (M/F) | 24/1 | 22/1
Median CD4 Cell Count | 6 | 9
Endpoints
CMV Retinitis Progression | 10 | 18
Discontinued Due to Adverse Event | 6 | 0
Withdrew Consent | 3 [One patient died 2 weeks after withdrawing consent.] | 1
Discontinued Due to Intercurrent Illness | 2 [Two patients on immediate therapy were diagnosed with CMV disease and discontinued from study. One patient on delayed therapy was diagnosed with CMV gastrointestinal disease.] | 1
Discontinued Based on Ophthalmological Examination | 1 [CMV retinitis progression not confirmed by retinal photography.] | 1
No Progression at Study Completion | 1 | 0
Not Evaluable at Baseline | 2 | 2

Dose-response study of VISTIDE (Study 107)

In an open-label trial, 100 patients with relapsing CMV retinitis were randomized to receive 5 mg/kg once a week for 2 weeks and then either 5 mg/kg (n = 49) or 3 mg/kg (n = 51) every other week. Enrolled patients had been diagnosed with CMV retinitis an average of 390 days prior to randomization and had received a median of 3.8 prior courses of systemic CMV therapy. Eighty-four of the 100 patients were considered evaluable for progression by serial retinal photographs (43 randomized to 5 mg/kg and 41 randomized to 3 mg/kg). Twenty-six and 21 patients discontinued therapy due to either an adverse event, intercurrent illness, excluded medication, or withdrawn consent in the 5 mg/kg and 3 mg/kg groups, respectively. Thirty-eight of the 100 randomized patients had progressed according to masked assessment of serial retinal photographs (13 randomized to 5 mg/kg and 25 randomized to 3 mg/kg). Using retinal photographs, the median (95% CI) times to retinitis progression for the 5 mg/kg and 3 mg/kg groups were 115 days (70, not reached) and 49 days (35, 52), respectively. This difference was statistically significant. Similar to Study 106, the median time to retinitis progression for the 5 mg/kg group was difficult to precisely estimate due to the limited number of patients remaining on treatment over time (4 of the 49 patients in the 5 mg/kg group were treated for 115 days or longer). Median (95% CI) times to the alternative endpoint of retinitis progression or study drug discontinuation were 49 days (38, 63) and 35 days (27, 39) for the 5 mg/kg and 3 mg/kg groups, respectively. This difference was statistically significant.

CONTRAINDICATIONS

Initiation of therapy with VISTIDE is contraindicated in patients with a serum creatinine > 1.5 mg/dL, a calculated creatinine clearance ≤ 55 mL/min, or a urine protein ≥ 100 mg/dL (equivalent to ≥ 2+ proteinuria).

VISTIDE is contraindicated in patients receiving agents with nephrotoxic potential. Such agents must be discontinued at least seven days prior to starting therapy with VISTIDE.

VISTIDE is contraindicated in patients with hypersensitivity to cidofovir.

VISTIDE is contraindicated in patients with a history of clinically severe hypersensitivity to probenecid or other sulfa-containing medications.

Direct intraocular injection of VISTIDE is contraindicated; direct injection of cidofovir has been associated with iritis, ocular hypotony, and permanent impairment of vision.

WARNINGS

Nephrotoxicity

Dose-dependent nephrotoxicity is the major dose-limiting toxicity related to VISTIDE administration. Cases of acute renal failure resulting in dialysis and/or contributing to death have occurred with as few as one or two doses of VISTIDE. Renal function (serum creatinine and urine protein) must be monitored within 48 hours prior to each dose of VISTIDE. Dose adjustment or discontinuation is required for changes in renal function (serum creatinine and/or urine protein) while on therapy. Proteinuria, as measured by urinalysis in a clinical laboratory, may be an early indicator of VISTIDE-related nephrotoxicity. Continued administration of VISTIDE may lead to additional proximal tubular cell injury, which may result in glycosuria, decreases in serum phosphate, uric acid, and bicarbonate, elevations in serum creatinine, and/or acute renal failure, in some cases, resulting in the need for dialysis. Patients with these adverse events occurring concurrently and meeting a criteria of Fanconi's syndrome have been reported. Renal function that did not return to baseline after drug discontinuation has been observed in clinical studies of VISTIDE.

Intravenous normal saline hydration and oral probenecid must accompany each VISTIDE infusion. Probenecid is known to interact with the metabolism or renal tubular excretion of many drugs (see PRECAUTIONS). The safety of VISTIDE has not been evaluated in patients receiving other known potentially nephrotoxic agents, such as intravenous aminoglycosides (e.g., tobramycin, gentamicin, and amikacin), amphotericin B, foscarnet, intravenous pentamidine, vancomycin, and non-steroidal anti-inflammatory agents (see DOSAGE AND ADMINISTRATION).

Preexisting Renal Impairment

Initiation of therapy with VISTIDE is contraindicated in patients with a baseline serum creatinine > 1.5 mg/dL, a creatinine clearance ≤ 55 mL/min, or a urine protein ≥ 100 mg/dL (equivalent to ≥ 2+ proteinuria).

Hematological Toxicity

Neutropenia may occur during VISTIDE therapy. Neutrophil count should be monitored while receiving VISTIDE therapy.

Decreased Intraocular Pressure/Ocular Hypotony

Decreased intraocular pressure may occur during VISTIDE therapy, and in some instances has been associated with decreased visual acuity. Intraocular pressure should be monitored during VISTIDE therapy.

Metabolic Acidosis

Decreased serum bicarbonate associated with proximal tubule injury and renal wasting syndrome (including Fanconi's syndrome) have been reported in patients receiving VISTIDE (see ADVERSE REACTIONS). Cases of metabolic acidosis in association with liver dysfunction and pancreatitis resulting in death have been reported in patients receiving VISTIDE.

PRECAUTIONS

General

Due to the potential for increased nephrotoxicity, doses greater than the recommended dose must not be administered and the frequency or rate of administration must not be exceeded (see DOSAGE AND ADMINISTRATION).

VISTIDE is formulated for intravenous infusion only and must not be administered by intraocular injection. Administration of VISTIDE by infusion must be accompanied by oral probenecid and intravenous saline prehydration (see DOSAGE AND ADMINISTRATION).

Uveitis/Iritis

Uveitis or iritis was reported in clinical trials and during postmarketing in patients receiving VISTIDE therapy. Treatment with topical corticosteroids with or without topical cycloplegic agents should be considered. Patients should be monitored for signs and symptoms of uveitis/iritis during VISTIDE therapy.

Information for Patients

Patients should be advised that VISTIDE is not a cure for CMV retinitis, and that they may continue to experience progression of retinitis during and following treatment. Patients receiving VISTIDE should be advised to have regular follow-up ophthalmologic examinations. Patients may also experience other manifestations of CMV disease despite VISTIDE therapy.

HIV-infected patients may continue taking antiretroviral therapy, but those taking zidovudine should be advised to temporarily discontinue zidovudine administration or decrease their zidovudine dose by 50%, on days of VISTIDE administration only, because probenecid reduces metabolic clearance of zidovudine.

Patients should be informed of the major toxicity of VISTIDE, namely renal impairment, and that dose modification, including reduction, interruption, and possibly discontinuation, may be required. Close monitoring of renal function (routine urinalysis and serum creatinine) while on therapy should be emphasized.

The importance of completing a full course of probenecid with each VISTIDE dose should be emphasized. Patients should be warned of potential adverse events caused by probenecid (e.g., headache, nausea, vomiting, and hypersensitivity reactions). Hypersensitivity/allergic reactions may include rash, fever, chills and anaphylaxis. Administration of probenecid after a meal or use of antiemetics may decrease the nausea. Prophylactic or therapeutic antihistamines and/or acetaminophen can be used to ameliorate hypersensitivity reactions.

Patients should be advised that cidofovir causes tumors, primarily mammary adenocarcinomas, in rats. VISTIDE should be considered a potential carcinogen in humans (See Carcinogenesis, Mutagenesis, & Impairment of Fertility). Women should be advised of the limited enrollment of women in clinical trials of VISTIDE.

Patients should be advised that VISTIDE caused reduced testes weight and hypospermia in animals. Such changes may occur in humans and cause infertility. Women of childbearing potential should be advised that cidofovir is embryotoxic in animals and should not be used during pregnancy. Women of childbearing potential should be advised to use effective contraception during and for 1 month following treatment with VISTIDE. Men should be advised to practice barrier contraceptive methods during and for 3 months after treatment with VISTIDE.

Drug Interactions

Probenecid

Probenecid is known to interact with the metabolism or renal tubular excretion of many drugs (e.g., acetaminophen, acyclovir, angiotensin-converting enzyme inhibitors, aminosalicylic acid, barbiturates, benzodiazepines, bumetanide, clofibrate, methotrexate, famotidine, furosemide, nonsteroidal anti-inflammatory agents, theophylline, and zidovudine). Concomitant medications should be carefully assessed. Zidovudine should either be temporarily discontinued or decreased by 50% when coadministered with probenecid on the day of VISTIDE infusion.

Nephrotoxic agents

Concomitant administration of VISTIDE and agents with nephrotoxic potential [e.g., intravenous aminoglycosides (e.g., tobramycin, gentamicin, and amikacin), amphotericin B, foscarnet, intravenous pentamidine, vancomycin, and nonsteroidal anti-inflammatory agents] is contraindicated. Such agents must be discontinued at least seven days prior to starting therapy with VISTIDE.

Carcinogenesis, Mutagenesis, & Impairment of Fertility

Chronic, two-year carcinogenicity studies in rats and mice have not been carried out to evaluate the carcinogenic potential of cidofovir. However, a 26-week toxicology study evaluating once weekly subscapular subcutaneous injections of cidofovir in rats was terminated at 19 weeks because of the induction, in females, of palpable masses, the first of which was detected after six doses. The masses were diagnosed as mammary adenocarcinomas which developed at doses as low as 0.6 mg/kg/week, equivalent to 0.04 times the human systemic exposure at the recommended intravenous VISTIDE dose based on AUC comparisons.

In a 26-week intravenous toxicology study in which rats received 0.6, 3, or 15 mg/kg cidofovir once weekly, a significant increase in mammary adenocarcinomas in female rats as well as a significant incidence of Zymbal's gland carcinomas in male and female rats were seen at the high dose but not at the lower two doses. The high dose was equivalent to 1.1 times the human systemic exposure at the recommended dose of VISTIDE, based on comparisons of AUC measurements. In light of the results of these studies, cidofovir should be considered to be a carcinogen in rats as well as a potential carcinogen in humans.

Cynomolgus monkeys received intravenous cidofovir, alone and in conjunction with concomitant oral probenecid, intravenously once weekly for 52 weeks at doses resulting in exposures of approximately 0.7 times the human systemic exposure at the recommended dose of VISTIDE. No tumors were detected. However, the study was not designed as a carcinogenicity study due to the small number of animals at each dose and the short duration of treatment.

No mutagenic response was observed in microbial mutagenicity assays involving Salmonella typhimurium (Ames) and Escherichia coli in the presence and absence of metabolic activation. An increase in micronucleated polychromatic erythrocytes in vivo was seen in mice receiving ≥ 2000 mg/kg, a dosage approximately 65-fold higher than the maximum recommended clinical intravenous VISTIDE dose based on body surface area estimations. Cidofovir induced chromosomal aberrations in human peripheral blood lymphocytes in vitro without metabolic activation. At the 4 cidofovir levels tested, the percentage of damaged metaphases and number of aberrations per cell increased in a concentration-dependent manner.

Studies showed that cidofovir caused inhibition of spermatogenesis in rats and monkeys. However, no adverse effects on fertility or reproduction were seen following once weekly intravenous injections of cidofovir in male rats for 13 consecutive weeks at doses up to 15 mg/kg/week (equivalent to 1.1 times the recommended human dose based on AUC comparisons). Female rats dosed intravenously once weekly at 1.2 mg/kg/week (equivalent to 0.09 times the recommended human dose based on AUC) or higher, for up to 6 weeks prior to mating and for 2 weeks post mating had decreased litter sizes and live births per litter and increased early resorptions per litter. Peri- and post-natal development studies in which female rats received subcutaneous injections of cidofovir once daily at doses up to 1.0 mg/kg/day from day 7 of gestation through day 21 postpartum (approximately 5 weeks) resulted in no adverse effects on viability, growth, behavior, sexual maturation or reproductive capacity in the offspring.

Pregnancy

Category C

Cidofovir was embryotoxic (reduced fetal body weights) in rats at 1.5 mg/kg/day and in rabbits at 1.0 mg/kg/day, doses which were also maternally toxic, following daily intravenous dosing during the period of organogenesis. The no-observable-effect levels for embryotoxicity in rats (0.5 mg/kg/day) and in rabbits (0.25 mg/kg/day) were approximately 0.04 and 0.05 times the clinical dose (5 mg/kg every other week) based on AUC, respectively. An increased incidence of fetal external, soft tissue and skeletal anomalies (meningocele, short snout, and short maxillary bones) occurred in rabbits at the high dose (1.0 mg/kg/day) which was also maternally toxic. There are no adequate and well-controlled studies in pregnant women. VISTIDE should be used during pregnancy only if the potential benefit justifies the potential risk to the fetus.

Nursing Mothers

It is not known whether cidofovir is excreted in human milk. Since many drugs are excreted in human milk and because of the potential for adverse reactions as well as the potential for tumorigenicity shown for cidofovir in animal studies, VISTIDE should not be administered to nursing mothers. The U.S. Public Health Service Centers for Disease Control and Prevention advises HIV-infected women not to breast-feed to avoid postnatal transmission of HIV to a child who may not yet be infected.

Pediatric Use

Safety and effectiveness in children have not been studied. The use of VISTIDE in children with AIDS warrants extreme caution due to the risk of long-term carcinogenicity and reproductive toxicity. Administration of VISTIDE to children should be undertaken only after careful evaluation and only if the potential benefits of treatment outweigh the risks.

Geriatric Use

No studies of the safety or efficacy of VISTIDE in patients over the age of 60 have been conducted. Since elderly individuals frequently have reduced glomerular filtration, particular attention should be paid to assessing renal function before and during VISTIDE administration (see DOSAGE AND ADMINISTRATION).

ADVERSE REACTIONS

1. Nephrotoxicity: Renal toxicity, as manifested by ≥ 2+ proteinuria, serum creatinine elevations of ≥ 0.4 mg/dL, or decreased creatinine clearance ≤ 55 mL/min, occurred in 79 of 135 (59%) patients receiving VISTIDE at a maintenance dose of 5 mg/kg every other week. Maintenance dose reductions from 5 mg/kg to 3 mg/kg due to proteinuria or serum creatinine elevations were made in 12 of 41 (29%) patients who had not received prior therapy for CMV retinitis (Study 106) and in 19 of 74 (26%) patients who had received prior therapy for CMV retinitis (Study 107). Prior foscarnet use has been associated with an increased risk of nephrotoxicity; therefore, such patients must be monitored closely (see CONTRAINDICATIONS, WARNINGS, DOSAGE AND ADMINISTRATION).
2. Neutropenia: In clinical trials, at the 5 mg/kg maintenance dose, a decrease in absolute neutrophil count to ≤ 500 cells/mm^3 occurred in 24% of patients. Granulocyte colony stimulating factor (GCSF) was used in 39% of patients.
3. Decreased Intraocular Pressure/Ocular Hypotony: Among the subset of patients monitored for intraocular pressure changes, a ≥ 50% decrease from baseline intraocular pressure was reported in 17 of 70 (24%) patients at the 5 mg/kg maintenance dose. Severe hypotony (intraocular pressure of 0–1 mm Hg) has been reported in 3 patients. Risk of ocular hypotony may be increased in patients with preexisting diabetes mellitus.
4. Anterior Uveitis/Iritis: Uveitis or iritis has been reported in clinical trials and during postmarketing in patients receiving VISTIDE therapy. Uveitis or iritis was reported in 15 of 135 (11%) patients receiving 5 mg/kg maintenance dosing. Treatment with topical corticosteroids with or without topical cycloplegic agents may be considered. Patients should be monitored for signs and symptoms of uveitis/iritis during VISTIDE therapy.
5. Metabolic Acidosis: A diagnosis of Fanconi's syndrome, as manifested by multiple abnormalities of proximal renal tubular function, was reported in 1% of patients. Decreases in serum bicarbonate to ≤ 16 mEq/L occurred in 16% of cidofovir-treated patients. Cases of metabolic acidosis in association with liver dysfunction and pancreatitis resulting in death have been reported in patients receiving VISTIDE.

In clinical trials, VISTIDE was withdrawn due to adverse events in 39% of patients treated with 5 mg/kg every other week as maintenance therapy.

The incidence of adverse reactions reported as serious in three controlled clinical studies in patients with CMV retinitis, regardless of presumed relationship to drug, is listed in Table 4.

Table 4. Serious Clinical Adverse Events or Laboratory Abnormalities Occurring in > 5% of Patients
 | N = 135 [Patients receiving 5 mg/kg maintenance regimen in Studies 105, 106 and 107.] # patients (%)
Proteinuria (≥ 100 mg/dL) | 68 | (50)
Neutropenia (≤ 500 cells/mm^3) | 33 | (24)
Decreased Intraocular Pressure [Defined as decreased intraocular pressure (IOP) to ≤ 50% that at baseline. Based on 70 patients receiving 5 mg/kg maintenance dosing (Studies 105, 106 and 107), for whom baseline and follow-up IOP determinations were recorded.] | 17 | (24)
Decreased Serum Bicarbonate (≤ 16 mEq/L) | 21 | (16)
Fever | 19 | (14)
Infection | 16 | (12)
Creatinine Elevation (≥ 2.0 mg/dL) | 16 | (12)
Pneumonia | 12 | (9)
Dyspnea | 11 | (8)
Nausea with Vomiting | 10 | (7)

The most frequently reported adverse events regardless of relationship to study drugs (cidofovir or probenecid) or severity are shown in Table 5.

The following additional list of adverse events/intercurrent illnesses have been observed in clinical studies of VISTIDE and are listed below regardless of causal relationship to VISTIDE. Evaluation of these reports was difficult because of the diverse manifestations of the underlying disease and because most patients received numerous concomitant medicines.

Body as a Whole: abdominal pain, accidental injury, AIDS, allergic reaction, back pain, catheter blocked, cellulitis, chest pain, chills and fever, cryptococcosis, cyst, death, face edema, flu-like syndrome, hypothermia, injection site reaction, malaise, mucous membrane disorder, neck pain, overdose, photosensitivity reaction, sarcoma, sepsis

Cardiovascular System: cardiomyopathy, cardiovascular disorder, congestive heart failure, hypertension, hypotension, migraine, pallor, peripheral vascular disorder, phlebitis, postural hypotension, shock, syncope, tachycardia, vascular disorder, edema

Digestive System: cholangitis, colitis, constipation, esophagitis, dyspepsia, dysphagia, fecal incontinence, flatulence, gastritis, gastrointestinal hemorrhage, gingivitis, hepatitis, hepatomegaly, hepatosplenomegaly, jaundice, abnormal liver function, liver damage, liver necrosis, melena, pancreatitis, proctitis, rectal disorder, stomatitis, aphthous stomatitis, tongue discoloration, mouth ulceration, tooth caries

Endocrine System: adrenal cortex insufficiency

Hemic & Lymphatic System: hypochromic anemia, leukocytosis, leukopenia, lymphadenopathy, lymphoma like reaction, pancytopenia, splenic disorder, splenomegaly, thrombocytopenia, thrombocytopenic purpura

Metabolic & Nutritional System: cachexia, dehydration, edema, hypercalcemia, hyperglycemia, hyperkalemia, hyperlipemia, hypocalcemia, hypoglycemia, hypoglycemic reaction, hypokalemia, hypomagnesemia, hyponatremia, hypophosphatemia, hypoproteinemia, increased alkaline phosphatase, increased BUN, increased lactic dehydrogenase, increased SGOT, increased SGPT, peripheral edema, respiratory alkalosis, thirst, weight loss, weight gain

Musculoskeletal System: arthralgia, arthrosis, bone necrosis, bone pain, joint disorder, leg cramps, myalgia, myasthenia, pathological fracture

Nervous System: abnormal dreams, abnormal gait, acute brain syndrome, agitation, amnesia, anxiety, ataxia, cerebrovascular disorder, confusion, convulsion, delirium, dementia, depression, dizziness, drug dependence, dry mouth, encephalopathy, facial paralysis, hallucinations, hemiplegia, hyperesthesia, hypertonia, hypotony, incoordination, increased libido, insomnia, myoclonus, nervousness, neuropathy, paresthesia, personality disorder, somnolence, speech disorder, tremor, twitching, vasodilatation, vertigo

Respiratory System: asthma, bronchitis, epistaxis, hemoptysis, hiccup, hyperventilation, hypoxia, increased sputum, larynx edema, lung disorder, pharyngitis, pneumothorax, rhinitis, sinusitis

Skin & Appendages: acne, angioedema, dry skin, eczema, exfoliative dermatitis, furunculosis, herpes simplex, nail disorder, pruritus, rash, seborrhea, skin discoloration, skin disorder, skin hypertrophy, skin ulcer, sweating, urticaria

Special Senses: abnormal vision, amblyopia, blindness, cataract, conjunctivitis, corneal lesion, corneal opacity, diplopia, dry eyes, ear disorder, ear pain, eye disorder, eye pain, hyperacusis, iritis, keratitis, miosis, otitis externa, otitis media, refraction disorder, retinal detachment, retinal disorder, taste perversion, tinnitus, uveitis, visual field defect, hearing loss

Urogenital System: decreased creatinine clearance, dysuria, glycosuria, hematuria, kidney stone, mastitis, metorrhagia, nocturia, polyuria, prostatic disorder, toxic nephrophathy, urethritis, urinary casts, urinary incontinence, urinary retention, urinary tract infection

Table 5. All Clinical Adverse Events, Laboratory Abnormalities or Intercurrent Illnesses Regardless of Severity Occurring in > 15% of Patients
 | N = 115 [Patients receiving 5 mg/kg maintenance regimen in Studies 106 and 107.] # patients (%)
Any Adverse Event | 115 | (100)
Proteinuria (≥ 30 mg/dL) | 101 | (88)
Nausea +/- Vomiting | 79 | (69)
Fever | 67 | (58)
Neutropenia (< 750 cells/mm^3) | 50 | (43)
Asthenia | 50 | (43)
Headache | 34 | (30)
Rash | 34 | (30)
Infection | 32 | (28)
Alopecia | 31 | (27)
Diarrhea | 30 | (26)
Pain | 29 | (25)
Creatinine Elevation (> 1.5 mg/dL) | 28 | (24)
Anemia | 28 | (24)
Anorexia | 26 | (23)
Dyspnea | 26 | (23)
Chills | 25 | (22)
Increased Cough | 22 | (19)
Oral Moniliasis | 21 | (18)

Reporting of Adverse Reactions

Malignancies or serious adverse reactions that occur in patients who have received VISTIDE should be reported to Gilead in writing to the Director of Clinical Research, Gilead Sciences, Inc., 333 Lakeside Drive, Foster City, CA 94404 or by calling 1-800-GILEAD-5 (445-3235), or to FDA MedWatch 1-800-FDA-1088/fax 1-800-FDA-0178.

OVERDOSAGE

Two cases of cidofovir overdose have been reported. These patients received single doses of VISTIDE at 16.3 mg/kg and 17.4 mg/kg, respectively, with concomitant oral probenecid and intravenous hydration. In both cases, the patients were hospitalized and received oral probenecid (one gram three times daily) and vigorous intravenous hydration with normal saline for 3 to 5 days. Significant changes in renal function were not observed in either patient.

DOSAGE AND ADMINISTRATION

VISTIDE MUST NOT BE ADMINISTERED BY INTRAOCULAR INJECTION.

Dosage

THE RECOMMENDED DOSAGE, FREQUENCY, OR INFUSION RATE MUST NOT BE EXCEEDED. VISTIDE MUST BE DILUTED IN 100 MILLILITERS 0.9% (NORMAL) SALINE PRIOR TO ADMINISTRATION. TO MINIMIZE POTENTIAL NEPHROTOXICITY, PROBENECID AND INTRAVENOUS SALINE PREHYDRATION MUST BE ADMINISTERED WITH EACH VISTIDE INFUSION.

Induction Treatment

The recommended induction dose of VISTIDE for patients with a serum creatinine of ≤ 1.5 mg/dL, a calculated creatinine clearance > 55 mL/min, and a urine protein < 100 mg/dL (equivalent to < 2+ proteinuria) is 5 mg/kg body weight (given as an intravenous infusion at a constant rate over 1 hr) administered once weekly for two consecutive weeks. Because serum creatinine in patients with advanced AIDS and CMV retinitis may not provide a complete picture of the patient's underlying renal status, it is important to utilize the Cockcroft-Gault formula to more precisely estimate creatinine clearance (CrCl). As creatinine clearance is dependent on serum creatinine and patient weight, it is necessary to calculate clearance prior to initiation of VISTIDE. CrCl (mL/min) should be calculated according to the following formula:

Creatinine clearance for males = | [140-age (years)] × [body wt (kg)] 72 × [serum creatinine (mg/dL)]
Creatinine clearance for females = | [140-age (years)] × [body wt (kg)] × 0.85 72 × [serum creatinine (mg/dL)]

Maintenance Treatment

The recommended maintenance dose of VISTIDE is 5 mg/kg body weight (given as an intravenous infusion at a constant rate over 1 hr), administered once every 2 weeks.

Dose Adjustment

Changes in Renal Function During VISTIDE Therapy

The maintenance dose of VISTIDE must be reduced from 5 mg/kg to 3 mg/kg for an increase in serum creatinine of 0.3 – 0.4 mg/dL above baseline. VISTIDE therapy must be discontinued for an increase in serum creatinine of ≥ 0.5 mg/dL above baseline or development of ≥ 3+ proteinuria.

Preexisting Renal Impairment

VISTIDE is contraindicated in patients with a serum creatinine concentration > 1.5 mg/dL, a calculated creatinine clearance ≤ 55 mL/min, or a urine protein ≥ 100 mg/dL (equivalent to ≥ 2+ proteinuria).

Probenecid

Probenecid must be administered orally with each VISTIDE dose. Two grams must be administered 3 hr prior to the VISTIDE dose and one gram administered at 2 and again at 8 hr after completion of the 1 hr VISTIDE infusion (for a total of 4 grams).

Ingestion of food prior to each dose of probenecid may reduce drug-related nausea and vomiting. Administration of an antiemetic may reduce the potential for nausea associated with probenecid ingestion. In patients who develop allergic or hypersensitivity symptoms to probenecid, the use of an appropriate prophylactic or therapeutic antihistamine and/or acetaminophen should be considered (see CONTRAINDICATIONS).

Hydration

Patients must receive at least one liter of 0.9% (normal) saline solution intravenously with each infusion of VISTIDE. The saline solution should be infused over a 1–2 hr period immediately before the VISTIDE infusion. Patients who can tolerate the additional fluid load should receive a second liter. If administered, the second liter of saline should be initiated either at the start of the VISTIDE infusion or immediately afterwards, and infused over a 1 to 3 hr period.

Method of Preparation and Administration

Inspect vials visually for particulate matter and discoloration prior to administration. If particulate matter or discoloration is observed, the vial should not be used. With a syringe, extract the appropriate volume of VISTIDE from the vial and transfer the dose to an infusion bag containing 100 mL 0.9% (normal) saline solution. Infuse the entire volume intravenously into the patient at a constant rate over a 1 hr period. Use of a standard infusion pump for administration is recommended.

It is recommended that VISTIDE infusion admixtures be administered within 24 hr of preparation and that refrigerator or freezer storage not be used to extend this 24 hr limit.

If admixtures are not intended for immediate use, they may be stored under refrigeration (2–8°C) for no more than 24 hr. Refrigerated admixtures should be allowed to equilibrate to room temperature prior to use.

The chemical stability of VISTIDE admixtures was demonstrated in polyvinyl chloride composition and ethylene/propylene copolymer composition commercial infusion bags, and in glass bottles. No data are available to support the addition of other drugs or supplements to the cidofovir admixture for concurrent administration.

VISTIDE is supplied in single-use vials. Partially used vials should be discarded (see Handling and Disposal).

Compatibility with Ringer's solution, Lactated Ringer's solution or bacteriostatic infusion fluids has not been evaluated.

Handling and Disposal

Due to the mutagenic properties of cidofovir, adequate precautions including the use of appropriate safety equipment are recommended for the preparation, administration, and disposal of VISTIDE. The National Institutes of Health presently recommends that such agents be prepared in a Class II laminar flow biological safety cabinet and that personnel preparing drugs of this class wear surgical gloves and a closed front surgical-type gown with knit cuffs. If VISTIDE contacts the skin, wash membranes and flush thoroughly with water. Excess VISTIDE and all other materials used in the admixture preparation and administration should be placed in a leak-proof, puncture-proof container. The recommended method of disposal is high temperature incineration.

Patient Monitoring

Serum creatinine and urine protein must be monitored within 48 hours prior to each dose. White blood cell counts with differential should be monitored prior to each dose. In patients with proteinuria, intravenous hydration should be administered and the test repeated. Intraocular pressure, visual acuity and ocular symptoms should be monitored periodically.

HOW SUPPLIED

VISTIDE (cidofovir injection) 75 mg/mL for intravenous infusion, is supplied as a non-preserved solution in single-use clear glass vials as follows:

NDC 61958-0101-1 375 mg in a 5 mL vial in a single-unit carton

STORAGE AND HANDLING

VISTIDE should be stored at controlled room temperature 20–25 °C (68–77 °F).

VISTIDE® (cidofovir injection) is covered by U.S. Patent No. 5,142,051 and its foreign counterparts. Other patents pending.

REFERENCES

1. Ho HT, Woods KL, Bronson JJ, De Boeck H, Martin JC and Hitchcock MJM. Intracellular Metabolism of the Antiherpesvirus Agent (S)-1-[3-hydroxy-2-(phosphonylmethoxy) propyl]cytosine. Mol Pharmacol 41:197–202, 1992.
2. Cherrington JM, Allen SJW, McKee BH, and Chen MS. Kinetic Analysis of the Interaction Between the Diphosphate of (S)-1-(3-hydroxy-2-phosphonylmethoxypropyl)cytosine, zalcitabineTP, zidovudineTP, and FIAUTP with Human DNA Polymerases b and g. Biochem Pharmacol 48:1986–1988, 1994.
3. Xiong X, Smith JL, Kim C, Huang E, and Chen MS. Kinetic Analysis of the Interaction of Cidofovir Diphosphate with Human Cytomegalovirus DNA Polymerase. Biochem Pharmacol 51:1563–1567, 1996.
4. Cherrington JM, Mulato AS, Fuller MD, Chen MS. In Vitro Selection of a Human Cytomegalovirus (HCMV) that is Resistant to Cidofovir. 35th International Conference on Antimicrobial Agents and Chemotherapy (ICAAC), San Francisco, CA. Abstract H117, 1995.
5. Stanat SC, Reardon JE, Erice A, Jordan MC, Drew WL, and Biron KK. Ganciclovir-Resistant Cytomegalovirus Clinical Isolates: Mode of Resistance to Ganciclovir. Antimicrob Agents Chemother 35:2191–2197, 1991.
6. Sullivan V, Biron KK, Talarico C, Stanat SC, Davis M, Pozzi M, and Coen DM. A Point Mutation in the Human Cytomegalovirus DNA Polymerase Gene Confers Resistance to Ganciclovir and phosphonylmethoxyalkyl Derivatives. Antimicrob Agents Chemother 37:19–25, 1993.
7. Tatarowicz WA, Lurain NS, and Thompson KD. A Ganciclovir-Resistant Clinical Isolate of Human Cytomegalovirus Exhibiting Cross-Resistance to other DNA Polymerase Inhibitors. J Infect Dis 166:904–907, 1992.
8. Lurain NS, Thompson KD, Holmes EW, and Read GS. Point Mutations in the DNA Polymerase Gene of Human Cytomegalovirus that Result in Resistance to Antiviral Agents. J Virol 66:7146–7152, 1992.
9. Smith IL, Cherrington JM, Jiles RE, Fuller MD, Freeman WR, Spector SA. High-level Resistance of Cytomegalovirus to Ganciclovir is Associated with Alterations in both the UL97 and DNA Polymerase Genes. J Infect Dis 176:69–77, 1997.
10. Sullivan V and Coen DM. Isolation of Foscarnet-Resistant Human Cytomegalovirus Patterns of Resistance and Sensitivity to Other Antiviral Drugs. J Infect Dis 164:781–784, 1991.
11. Snoeck R, Andrei G, and De Clercq E. Patterns of Resistance and Sensitivity to Antiviral Compounds of Drug-Resistant Strains of Human Cytomegalovirus Selected in Vitro. Eur J Clin Microbiol Infect Dis 15:574–579, 1996.
12. Baldanti F, Underwood MR, Stanat SC, Biron KK, Chou S, Sarasini A, Silini E, and Gerna G. Single Amino Acid Changes in the DNA Polymerase Confer Foscarnet Resistance and Slow-Growth Phenotype, While Mutations in the UL97-Encoded Phosphotransferase Confer Ganciclovir Resistance in Three Double-Resistant Human Cytomegalovirus Strains Recovered from Patients with AIDS. J Virol 70:1390–1395, 1996.
13. The Studies of Ocular Complications of AIDS Research Group in Collaboration with the AIDS Clinical Trials Group. Cidofovir (HPMPC) for the Treatment of Cytomegalovirus Retinitis in Patients with AIDS: the HPMPC Peripheral Cytomegalovirus Retinitis Trial. Ann Intern Med 126:264–274, 1997.
14. Lalezari JP, Stagg RJ, Kupperman BD, et al. Intravenous Cidofovir for Peripheral Cytomegalovirus Retinitis in Patients with AIDS. A Randomized, Controlled Trial. Ann Intern Med 126:257–263, 1997.

September 2010

Manufactured for and distributed by:
Gilead Sciences, Inc.
Foster City, CA 94404

© 2010 Gilead Sciences, Inc. All rights reserved

20-638-GS-001

PRINCIPAL DISPLAY PANEL - 5 mL Vial Carton

NDC 61958-0101-1

Vistide®
(cidofovir injection)

Each 5 mL single-use vial contains
375 mg (75 mg/mL)
of cidofovir (anhydrous)

Rx only

DILUTE BEFORE USE

For Intravenous Infusion Only.
Not For Intraocular Injection.

GILEAD